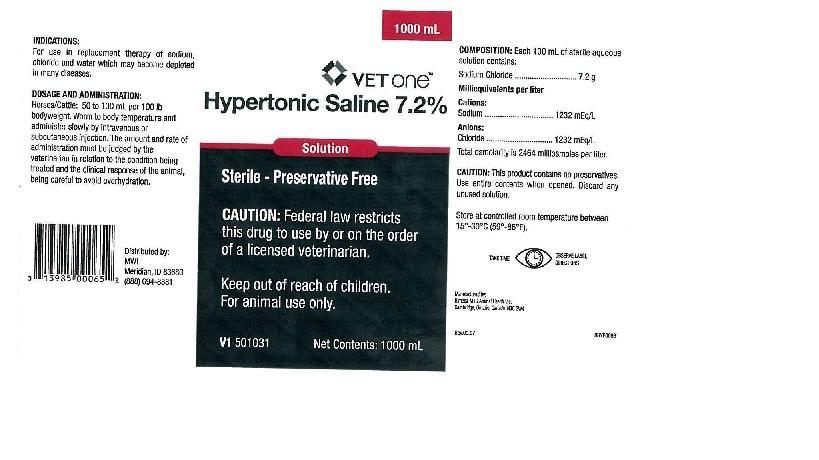 DRUG LABEL: Hypertonic Saline
NDC: 13985-031 | Form: INJECTION, SOLUTION
Manufacturer: MWI/VetOne
Category: animal | Type: PRESCRIPTION ANIMAL DRUG LABEL
Date: 20181211

ACTIVE INGREDIENTS: Sodium Chloride 7.2 g/100 mL

INDICATIONS:

For use in replacement therapy of sodium, chloride and water which may become depleted in many diseases.

DOSAGE AND ADMINISTRATION:

Horses/Cattle: 50 to 100 mL per 100 lb bodyweight. Warm to body temperature and administer slowly by intravenous or subcutaneous injection. The amount and rate of administration must be judged by the veterinarian in relation to the condition being treated and the clinical response of the animal, being careful to avoid overhydration.

DOSAGE FORMS AND STRENGTHS

COMPOSITION: Each 100 mL of sterile aqueous solution contains:

Sodium Chloride.............................7.2 g

Milliequivalents per liter

Cations:

Sodium.........................................1232mEq/L

Anions:

Chloride........................................1232mEq/L

Total osmolarity is 2464 milliomoles per liter.

PRECAUTIONS

CAUTION: This product contains no preservatives. Use entire contents when opened. Discard any unused solution.

STORAGE AND HANDLING

Store at controlled room temperature between 15 degrees - 30 degrees C (59 degrees - 86 degrees F)

PACKAGE LABEL

1000 mL

VETONE

Hypertonic Saline 7.2%

Solution

Sterile - Preservative Free

CAUTION: Federal law restricts this drug to use by or on the order of a licensed veterinarian.

Keep out of reach of children.

For animal use only.

Net Contents: 1000 mL